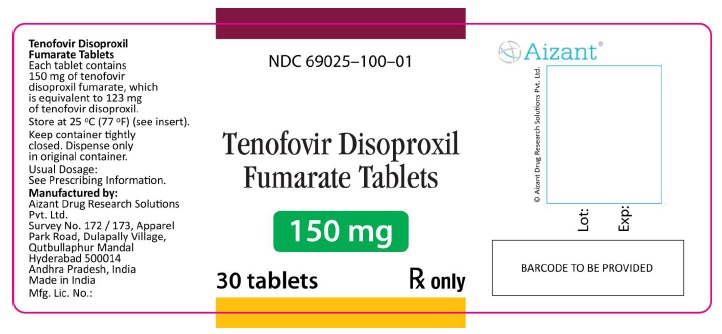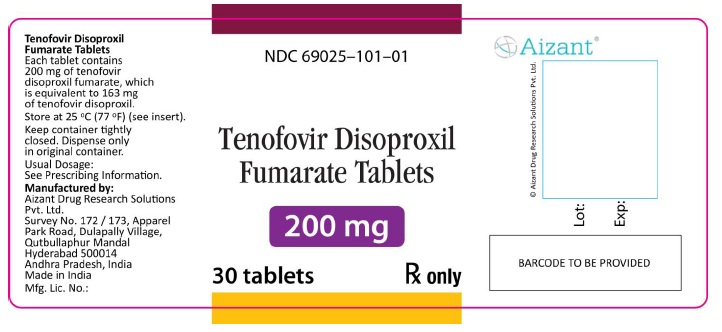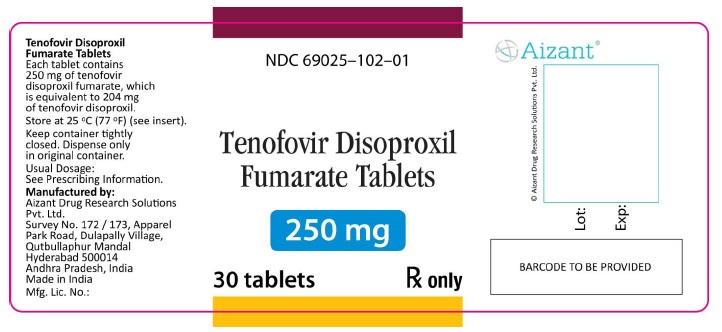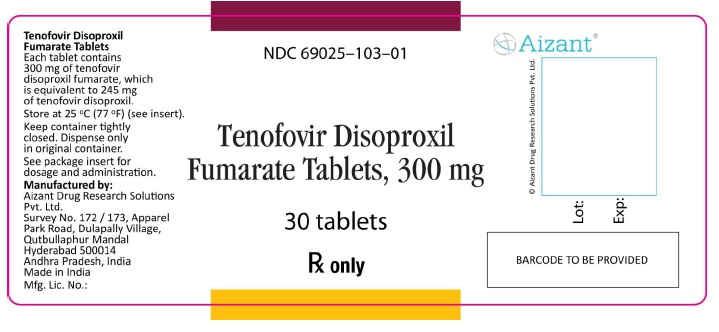 DRUG LABEL: tenofovir disoproxil fumarate
NDC: 69025-100 | Form: TABLET, FILM COATED
Manufacturer: AIZANT DRUG RESEARCH SOLUTIONS PVT LTD
Category: prescription | Type: HUMAN PRESCRIPTION DRUG LABEL
Date: 20150820

ACTIVE INGREDIENTS: tenofovir disoproxil fumarate 150 mg/1 1

These highlights do not include all the information needed to use Tenofovir disoproxil Fumarate Tablets safely and effectively. See full prescribing information for tenofovir disoproxil fumarate tablets.
Tenofovir disoproxil fumarate tablets, for oral use
Initial U.S. Approval: 2001

16 HOW SUPPLIED/STORAGE AND HANDLING

Tenofovir disoproxiltablets, 150 mg, are triangle-shaped, white, film-coated tablets containing 150 mg of tenofovirdisoproxilfumarate, which is equivalent to 123 mg of tenofovir disoproxil, are debossed with "100" onone side and "A" on the other side. Each bottle contains 30 tablets, a desiccant (1g silica gel canisteror sachet), and closed with a child-resistant closure. (NDC 69025-100-01)

Tenofovir disoproxiltablets, 200 mg, are round-shaped, white, film-coated tablets containing 200 mg of tenofovirdisoproxilfumarate, which is equivalent to 163 mg of tenofovir disoproxil, are debossed with "101" onone side and "A" on the other side. Each bottle contains 30 tablets, a desiccant (1g silica gelcanister or sachet), and closed with a child-resistant closure. (NDC 69025-101-01)

Tenofovir disoproxiltablets, 250 mg, are capsule-shaped, white, film-coated tablets containing 250 mg of tenofovirdisoproxilfumarate, which is equivalent to 204 mg of tenofovir disoproxil, are debossed with "102" onone side and "A" on the other side. Each bottle contains 30 tablets, a desiccant (1g silica gel canisteror sachet), and closed with a child-resistant closure. (NDC 69025-102-01)

Tenofovir disoproxiltablets, 300 mg, are almond-shaped, light blue, film-coated tablets containing 300 mg oftenofovir disoproxilfumarate, which is equivalent to 245 mg of tenofovir disoproxil, are debossedwith "103" on one side and "A" on the other side. Each bottle contains 30tablets, a desiccant (1g silica gel canister or sachet), and closed with a child-resistant closure. (NDC 69025-103-01)

PACKAGE LABEL

PRINCIPAL DISPLAY PANEL

Tenofovir Disoproxil Fumarate Tablets

NDC 69025-100-01

150 mg - 30 Tablets

Rx only

Tenofovir Disoproxil Fumarate Tablets

NDC 69025-101-01

200 mg - 30 Tablets

Rx only

Tenofovir Disoproxil Fumarate Tablets

NDC 69025-102-01

250 mg - 30 Tablets

Rx only

Tenofovir Disoproxil Fumarate Tablets

NDC 69025-103-01

300 mg - 30 Tablets

Rx only